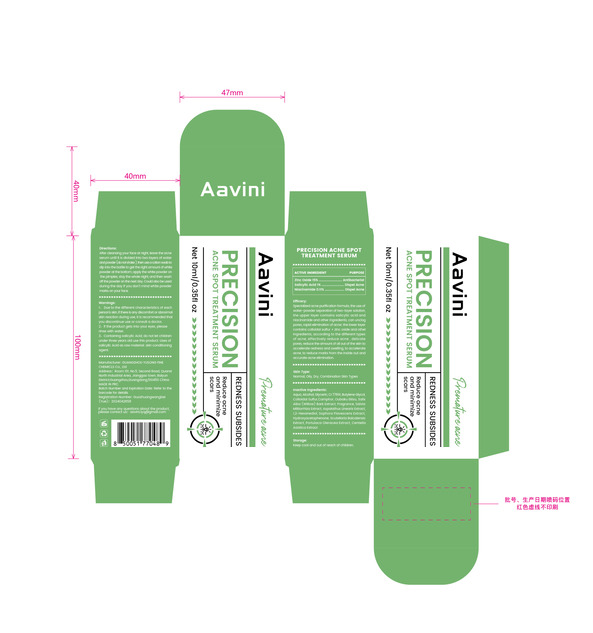 DRUG LABEL: Aavini Precision Acne Spot Treatment Serum
NDC: 84558-004 | Form: LIQUID
Manufacturer: GUANGZHOU YUSONG FINE CHEMICLS Co., Ltd
Category: otc | Type: HUMAN OTC DRUG LABEL
Date: 20241018

ACTIVE INGREDIENTS: SALICYLIC ACID 1 g/100 mL; NIACINAMIDE 0.11 g/100 mL; ZINC OXIDE 15 g/100 mL
INACTIVE INGREDIENTS: CENTELLA ASIATICA TRITERPENOIDS; HYDROXYACETOPHENONE; WATER; ALCOHOL; GLYCERIN; TITANIUM DIOXIDE; BUTYLENE GLYCOL; SULFUR; CAMPHORIC ACID; SALIX ALBA BARK; SCUTELLARIA BAICALENSIS ROOT; 1,2-HEXANEDIOL; PURSLANE

84558-004

Active Ingredient(s)

zinc Oxide 15%
salicylic Acid 1%
Niacinamide 0.11%

Purpose

Antibacterial
Dispel Acne
Dispel Acne

Use

Specialized acne purification formula, the use of water-powder separation of two-layer solution,
the upper layer contains salicylic acid and niacinamide and other ingredients, can unclog
pores, rapid elimination of acne; the lower layer contains colloidal sulfur + zinc oxide and other
ingredients, according to the different types of acne, effectively reduce acne, delicate
pores, reduce the amount of oil out of the skin to accelerate redness and swelling. to accelerate
acne, to reduce marks from the inside out and accurate acne elimination.

Warnings

1、Due to the different characteristics of each person's skin, if there is any discomfort or abnormal skin reaction during use, it is recommended that you discontinue use or consult a doctor.
2、if the product gets into your eyes, please rinse with water.
3、Containing salicylic Acid, do not let children under three years old use this product. Uses of salicylic Acid as raw material: skin conditioning agent.

Do not use

History of allergies or allergic reaction to any ingredient in this product, Please stop using immediately

WHEN USING

if the product gets into your eyes, please rinse with water.

STOP USE

Stop using immediately if there are any adverse reactions or discomfort

KEEP OUT OF REACH OF CHILDREN

Do not allow children under the age of three to use this product

Directions

After cleansing your face at night, leave the acne serum until it is divided into two layers of water
andpowder donotshake) thenuseacottonswabto dip into the bottle to get the right amount of white
powder at the bottom, apply the white powder on the pimples, stay the whole night and then wash
off the powder on the next day. Could also be used during the day if you don't mind white powder
marks on your face.

Other information

Keep cool and out of reach of children.

Inactive ingredients

Aqua, Alcohol, Glycerin, CI 77891 Butylene Glycol, Colloidal Sulfur.Camphor, Oubaku Ekisu,

Salix Alba (Willow) Bark Extract, Fragrance, Salvia Miltiorrhiza Extract, Aspalathus Linearis Extract,

1.2 -Hexanediol, Sophora Flavescens Extract, Hydroxyacetophenone. Scutellaria Baicalensis Extract,

Portulaca Oleracea Extract, Centella Asiatica Extract